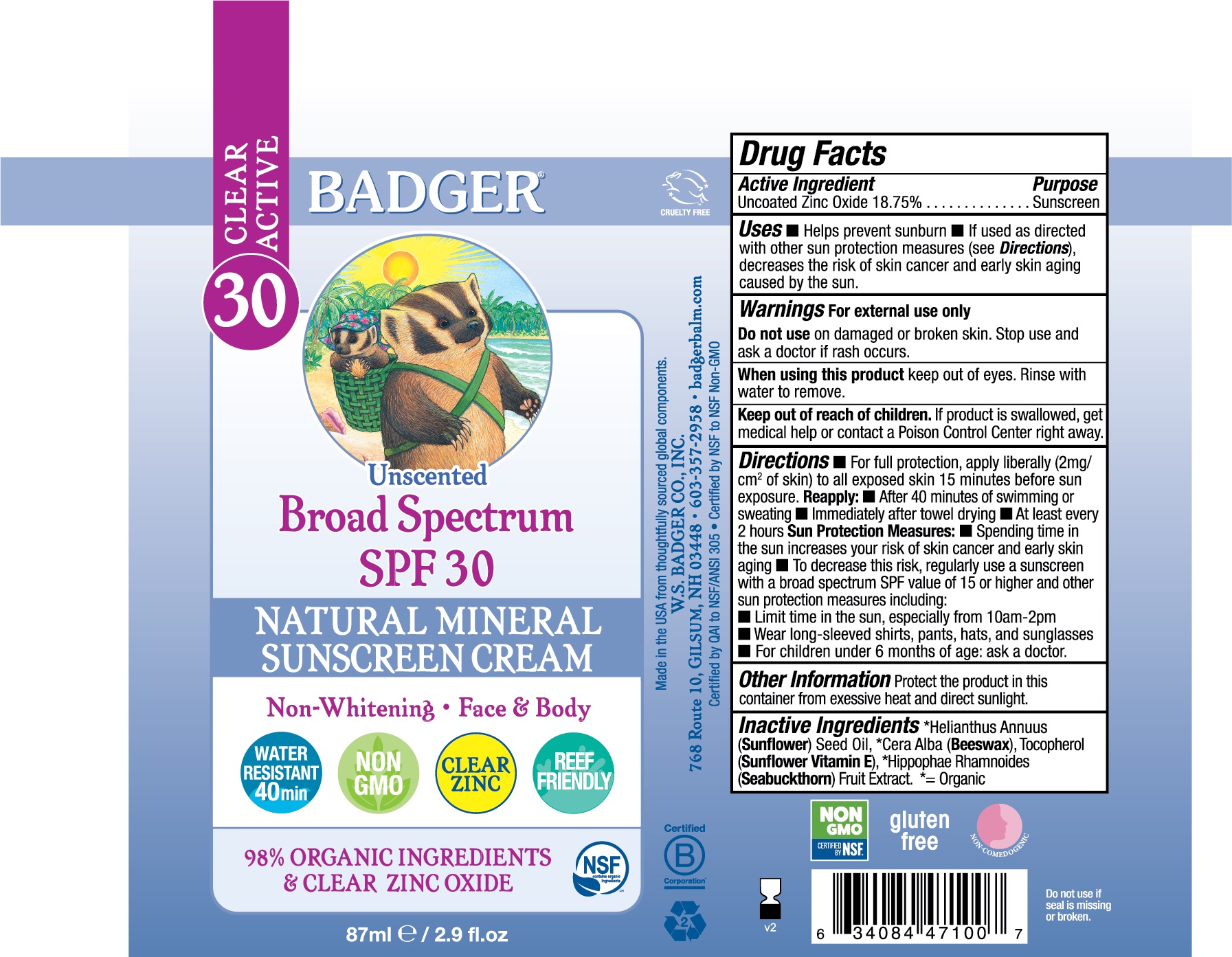 DRUG LABEL: Badger Active SPF 30 Clear Zinc Sunscreen
NDC: 62206-4710 | Form: CREAM
Manufacturer: W.S. Badger Company, Inc.
Category: otc | Type: HUMAN OTC DRUG LABEL
Date: 20210929

ACTIVE INGREDIENTS: ZINC OXIDE 18.75 g/100 mL
INACTIVE INGREDIENTS: SUNFLOWER OIL; YELLOW WAX; TOCOPHEROL; HIPPOPHAE RHAMNOIDES FRUIT

Badger® Active SPF 30 Clear Zinc Sunscreen Cream

Drug Facts

Active Ingredient

Uncoated Zinc Oxide 18.75%

Purpose

Sunscreen

Uses

- Helps prevent sunburn
- If used as directed with other sun protection measures (see Directions), decreases the risk of skin cancer and early skin aging caused by the sun.

Warnings

For external use only

Do not use on damaged or broken skin. Stop and ask a doctor if rash occurs.

When using this product keep out of eyes. Rinse with water to remove.

Keep out of reach of children. If product is swallowed, get medical help or contact a Poison Control Center right away.

Directions

- For full protection, apply liberally (2mg/cm^2 of skin) to all exposed skin 15 minutes before sun exposure, then rub in to reduce whitening effect.

Reapply:

- After 80 minutes of swimming or sweating
- Immediately after towel drying
- At least every 2 hours

Sun Protection Measures:

- Spending time in the sun increases your risk of skin cancer and early skin aging
- To decrease this risk, regularly use a sunscreen with a broad spectrum SPF value of 15 or higher and other sun protection measures including:
  - Limit time in the sun, especially from 10am-2pm
  - Wear long-sleeved shirts, pants, hats, and sunglasses
- For children under 6 months of age: ask a doctor.

Ingredients

[= Organic] Helianthus Annuus (Sunflower) Oil, Cera Alba (Beeswax), Tocopherol (Sunflower Vitamin E), * Hippophae rhamnoides (Sea Buckthorn) Fruit Extract.

Other Information

Store at temperatures below 90°F.

PRINCIPAL DISPLAY PANEL - 87 ml Tube Label

Active
BADGER ®

Unscented
Broad Spectrum
SPF 30

CLEAR ZINC

NATURAL MINERAL
SUNSCREEN CREAM

Non-Whitening

Face & Body

WATER RESISTANT 40min

NON GMO

CLEAR ZINC

REEF FRIENDLY

98% ORGANIC INGREDIENTS

& CLEAR ZINC OXIDE

87ml/2.9 fl.oz